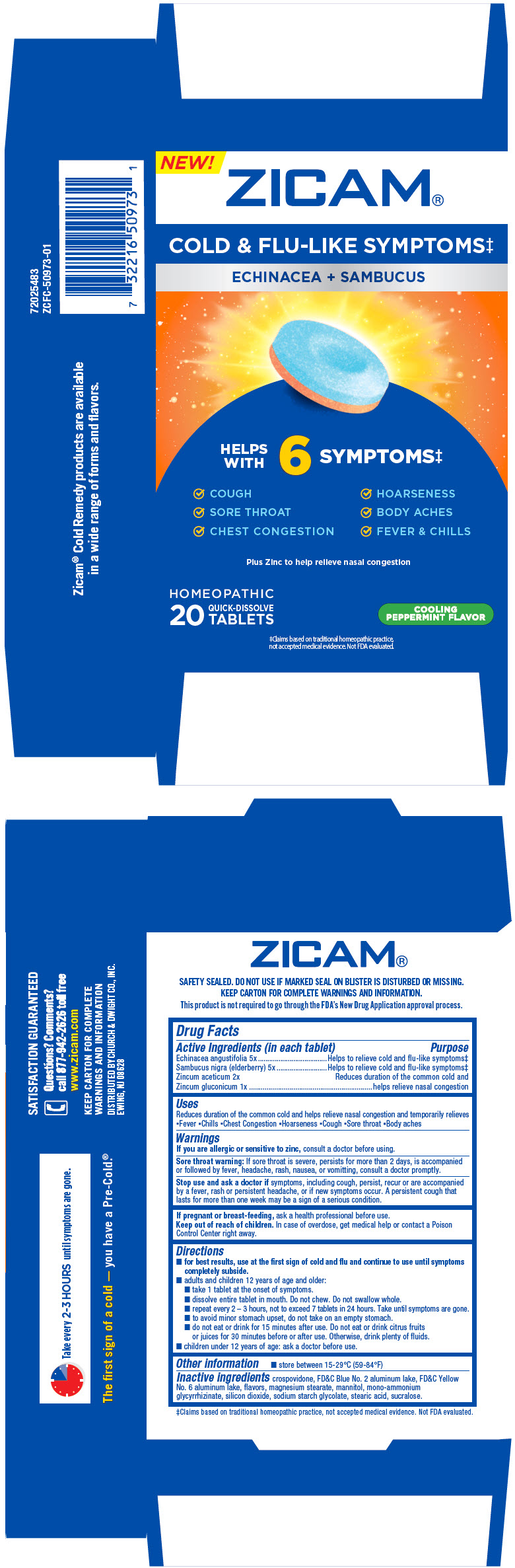 DRUG LABEL: zicam cold and flu-like symptoms
NDC: 10237-479 | Form: TABLET, MULTILAYER
Manufacturer: CHURCH & DWIGHT CO, INC.
Category: homeopathic | Type: HUMAN OTC DRUG LABEL
Date: 20251211

ACTIVE INGREDIENTS: ZINC ACETATE ANHYDROUS 2 [hp_X]/1 1; ZINC GLUCONATE 1 [hp_X]/1 1; ECHINACEA ANGUSTIFOLIA WHOLE 5 [hp_X]/1 1; SAMBUCUS NIGRA FLOWERING TOP 5 [hp_X]/1 1
INACTIVE INGREDIENTS: CROSPOVIDONE (120 .MU.M); FD&C BLUE NO. 2--ALUMINUM LAKE; FD&C YELLOW NO. 6; MANNITOL; AMMONIUM GLYCYRRHIZATE; MAGNESIUM STEARATE; SILICON DIOXIDE; SODIUM STARCH GLYCOLATE TYPE A POTATO; STEARIC ACID; SUCRALOSE

ZICAM®COLD & FLU-LIKE SYMPTOMS
Echinacea + Sambucus

Drug Facts

ACTIVE INGREDIENT

Active Ingredients (in each tablet) | Purpose
Echinacea angustifolia 5x | Helps to relieve cold and flu-like symptoms [Claims based on traditional homeopathic practice, not accepted medical evidence. Not FDA evaluated.]
Sambucus nigra (elderberry) 5x | Helps to relieve cold and flu-like symptoms
Zincum aceticum 2x Zincum gluconicum 1x | Reduces duration of the common cold and helps relieve nasal congestion

Uses

Reduces duration of the common cold and helps relieve nasal congestion and temporarily relieves

- Fever
- Chills
- Chest Congestion
- Hoarseness
- Cough
- Sore throat
- Body aches

Warnings

ASK DOCTOR

If you are allergic or sensitive to zinc,consult a doctor before using.

Sore throat warning

If sore throat is severe, persists for more than 2 days, is accompanied or followed by fever, headache, rash, nausea, or vomitting, consult a doctor promptly.

Stop use and ask a doctor ifsymptoms, including cough, persist, recur or are accompanied by a fever, rash or persistent headache, or if new symptoms occur. A persistent cough that lasts for more than one week may be a sign of a serious condition.

PREGNANCY OR BREAST FEEDING

If pregnant or breast-feeding,ask a health professional before use.

Keep out of reach of children.In case of overdose, get medical help or contact a Poison Control Center right away.

Directions

- for best results, use at the first sign of cold and flu and continue to use until symptoms completely subside.
- adults and children 12 years of age and older:
  - take 1 tablet at the onset of symptoms.
  - dissolve entire tablet in mouth. Do not chew. Do not swallow whole.
  - repeat every 2 – 3 hours, not to exceed 7 tablets in 24 hours. Take until symptoms are gone.
  - to avoid minor stomach upset, do not take on an empty stomach.
  - do not eat or drink for 15 minutes after use. Do not eat or drink citrus fruits or juices for 30 minutes before or after use. Otherwise, drink plenty of fluids.
- children under 12 years of age: ask a doctor before use.

Other information

- store between 15-29°C (59-84°F)

Inactive ingredients

crospovidone, FD&C Blue No. 2 aluminum lake, FD&C Yellow No. 6 aluminum lake, flavors, magnesium stearate, mannitol, mono-ammonium glycyrrhizinate, silicon dioxide, sodium starch glycolate, stearic acid, sucralose.

Questions? Comments?

call 877-942-2626 toll free

DISTRIBUTED BY CHURCH & DWIGHT CO., INC.
EWING, NJ 08628

PRINCIPAL DISPLAY PANEL - 20 Tablet Blister Pack Carton

NEW!
ZICAM®

COLD & FLU-LIKE SYMPTOMS‡

ECHINACEA + SAMBUCUS

HELPS
WITH
6
SYMPTOMS‡

✓ COUGH
✓ HOARSENESS

✓ SORE THROAT
✓ BODY ACHES

✓ CHEST CONGESTION
✓ FEVER & CHILLS

Plus Zinc to help relieve nasal congestion

HOMEOPATHIC

20
QUICK-DISSOLVE
TABLETS

COOLING
PEPPERMINT FLAVOR

‡Claims based on traditional homeopathic practice,
not accepted medical evidence. Not FDA evaluated.